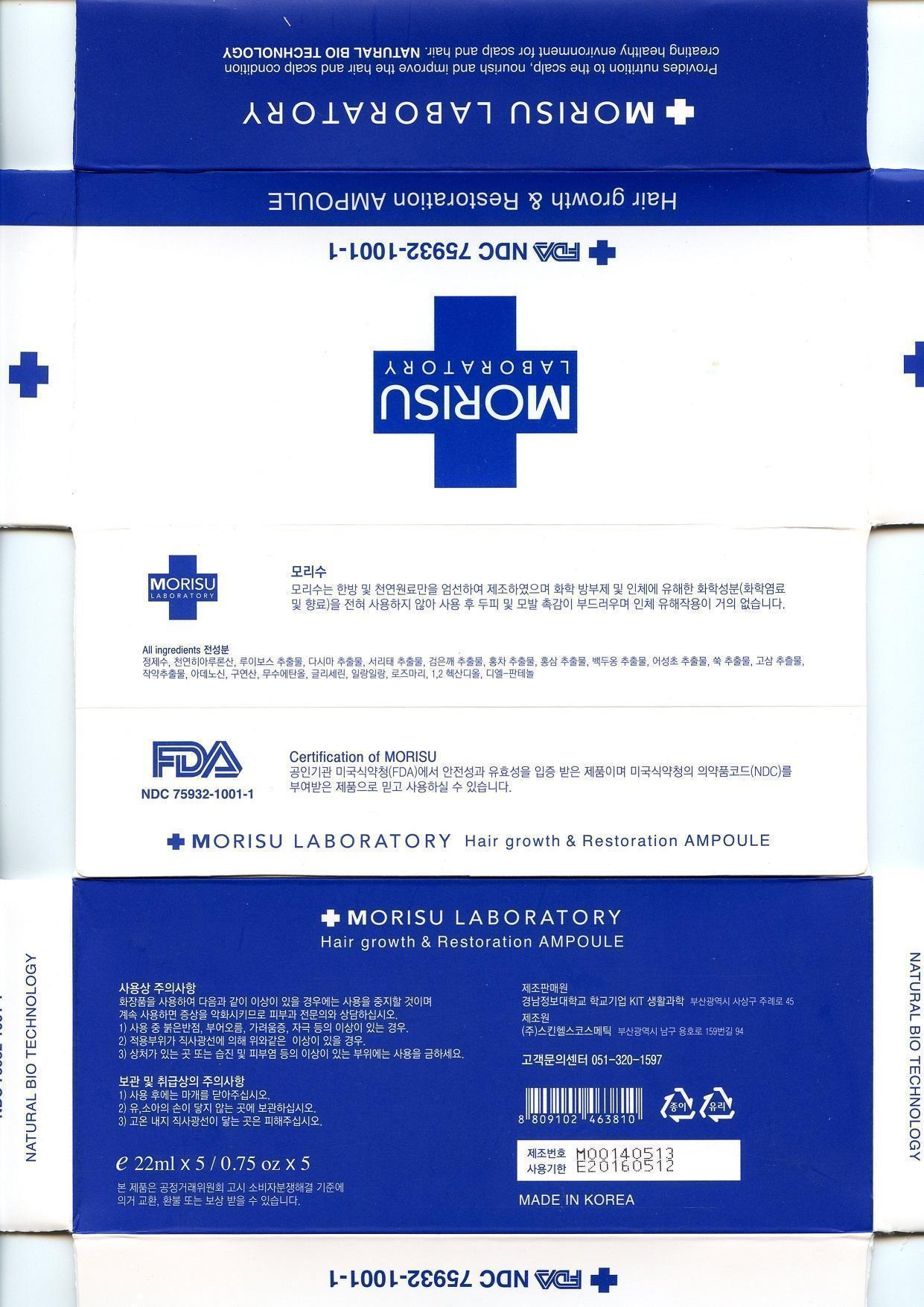 DRUG LABEL: MORISU
NDC: 75932-1002 | Form: SOLUTION
Manufacturer: Kyungnam College of Information & Technology
Category: otc | Type: HUMAN OTC DRUG LABEL
Date: 20150224

ACTIVE INGREDIENTS: HYALURONIC ACID 0.01 g/100 mL
INACTIVE INGREDIENTS: ASPALATHUS LINEARIS LEAF; CANANGA OIL; LEDUM PALUSTRE TWIG; GLYCERIN; CITRIC ACID MONOHYDRATE; WATER; ADENOSINE; SESAME OIL; ARTEMISIA PRINCEPS LEAF; HOUTTUYNIA CORDATA FLOWERING TOP; TEA LEAF

Drug Facts

active ingredient: adenosine

Inactive ingredient: Rooibos extract, black bean extract, black tea extract, mugwort extract, ylang ylang, rosemary, citric acid, anhydrous ethanol, water, sodium hyaluronate,

PURPOSE

for hair grower and loss prevention

keep out of reach of the children

INDICATIONS AND USAGE

- spray on the scalp 2~3 times daily as needed
- recommendable to apply enough on the scalp prior to going to bed

WARNINGS

- stop using and see a doctor if any hypersensitivity symptom continues
- avoid storing under direct sung light or high temperature

DOSAGE AND ADMINISTRATION

- for hair scalp spraying only